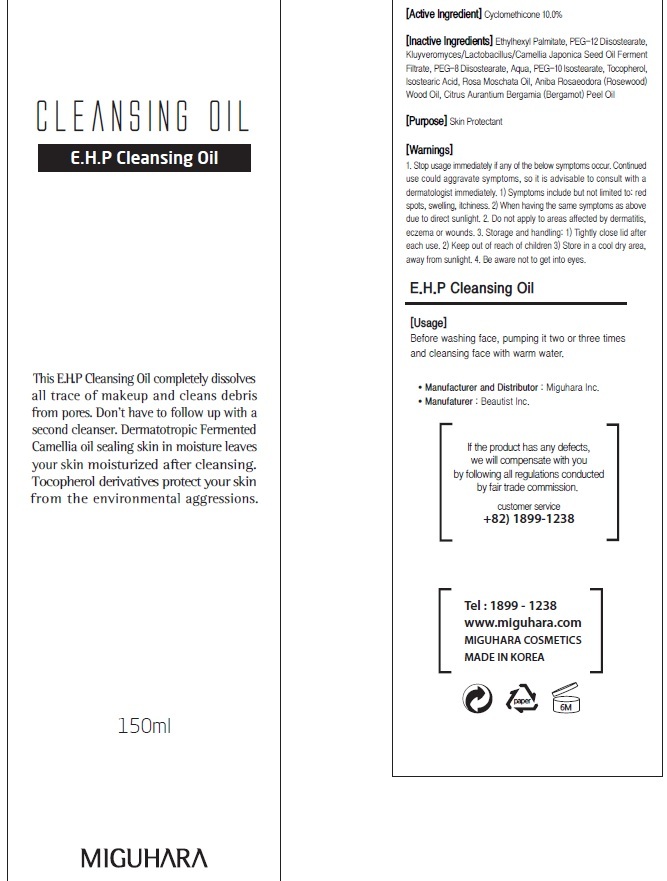 DRUG LABEL: EHP Cleansing
NDC: 70380-010 | Form: OIL
Manufacturer: MIGUHARA
Category: otc | Type: HUMAN OTC DRUG LABEL
Date: 20160218

ACTIVE INGREDIENTS: Cyclomethicone 15 g/150 mL
INACTIVE INGREDIENTS: Ethylhexyl Palmitate; PEG-12 Diisostearate

ACTIVE INGREDIENT

Active Ingredient: Cyclomethicone 10.0%

INACTIVE INGREDIENT

Inactive Ingredients: Ethylhexyl Palmitate, PEG-12 Diisostearate, Kluyveromyces/Lactobacillus/Camellia Japonica Seed Oil Ferment Filtrate, PEG-8 Diisostearate, Aqua, PEG-10 Isostearate, Tocopherol, Isostearic Acid, Rosa Moschata Oil, Aniba Rosaeodora (Rosewood) Wood Oil, Citrus Aurantium Bergamia (Bergamot) Peel Oil

PURPOSE

Purpose: Skin Protectant

WARNINGS

1. Stop usage immediately if any of the below symptoms occur. Continued use could aggravate symptoms, so it is advisable to consult with a dermatologist immediately. 1) Symptoms include but not limited to: red spots, swelling, itchiness. 2) When having the same symptoms as above due to direct sunlight. 2. Do not apply to areas affected by dermatitis, eczema or wounds. 3. Storage and handling: 1) Tightly close lid after each use. 2 Keep out of reach of children 3) Store in a cool dry area, away from sunlight 4. Be aware not to get into eyes.

KEEP OUT OF REACH OF CHILDREN

Usage

Usage: Before washing face, pumping it two or three times and cleansing face with warm water.

Usage

Usage: Before washing face, pumping it two or three times and cleansing face with warm water.